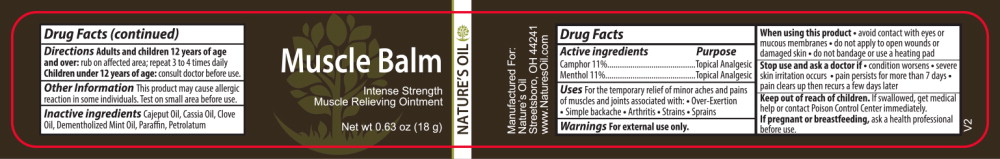 DRUG LABEL: Muscle Balm
NDC: 66902-142 | Form: OINTMENT
Manufacturer: Natural Essentials, Inc.
Category: otc | Type: HUMAN OTC DRUG LABEL
Date: 20241004

ACTIVE INGREDIENTS: MENTHOL, UNSPECIFIED FORM 110 mg/1 g; CAMPHOR (SYNTHETIC) 110 mg/1 g
INACTIVE INGREDIENTS: CAJUPUT OIL; CHINESE CINNAMON OIL; CLOVE OIL; PEPPERMINT OIL TERPENELESS; PARAFFIN; PETROLATUM

Drug Facts

Active ingredients

Camphor 11 %

Menthol 11%

Purpose

Topical Analgesic

Topical Analgesic

Uses

For the temporary relief of minor aches and pains of muscles and joints associated with:

- Over-Exertion
- Simple backache
- Arthritis
- Strains
- Sprains

Warnings

For external use only.

When using this product

- avoid contact with eyes or mucous membranes
- do not apply to open wounds or damaged skin
- do not bandage or use a heating pad

Stop use and ask a doctor if

- condition worsens
- severe skin irritation occurs
- pain persists for more than 7 days
- pain clears up then recurs a few days later

Keep out of reach of children.If swallowed, get medical help or contact Poison Control Center immediately.

PREGNANCY OR BREAST FEEDING

If pregnant or breastfeeding,ask a health professional before use.

Directions

Adults and children 12 years of age and over:rub on affected area; repeat 3 to 4 times daily

Children under 12 years of age:consult doctor before use.

Other Information

This product may cause allergic reaction in some individuals. Test on small area before use.

Inactive ingredients

Cajeput Oil, Cassia Oil, Clove Oil, Dementholized Mint Oil, Paraffin, Petrolatum

Principal Display Panel – 18 g Jar Label

NATURE'S OIL
Muscle Balm

Intense Strength

Muscle Relieving Ointment

Net wt 0.63 oz (18 g)